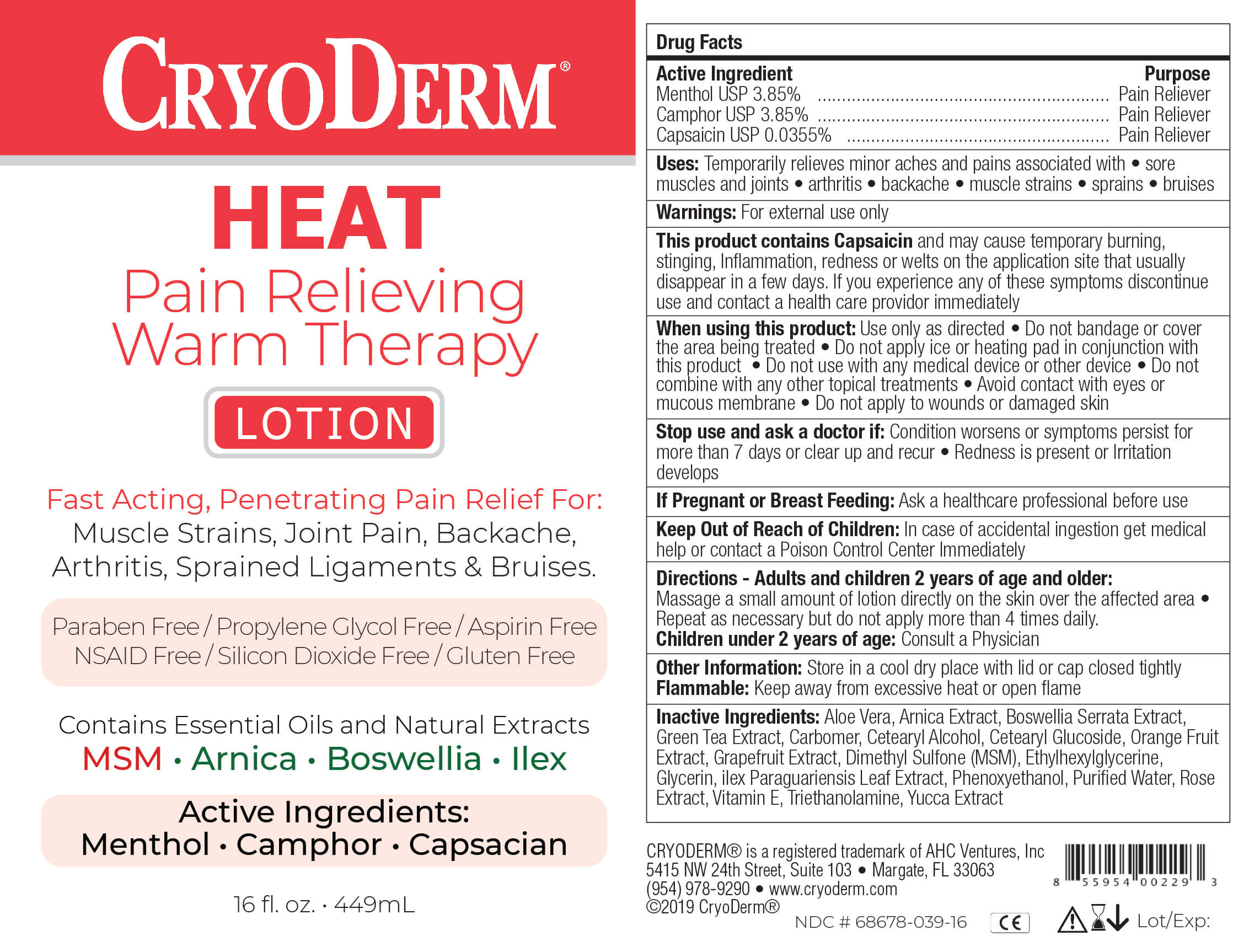 DRUG LABEL: Pain Relieving
NDC: 68678-039 | Form: LOTION
Manufacturer: AHC VENTURES CORP DBA CRY
Category: otc | Type: HUMAN OTC DRUG LABEL
Date: 20250902

ACTIVE INGREDIENTS: MENTHOL 3.85 g/100 mL; CAMPHOR (SYNTHETIC) 3.85 g/100 mL; CAPSAICIN 0.0355 g/100 mL
INACTIVE INGREDIENTS: WATER 77.3645 mL/100 mL; ALOE VERA LEAF 0.5 mL/100 mL; ARNICA MONTANA 0.5 mL/100 mL; BOSWELLIA SERRATA WHOLE 0.5 mL/100 mL; GREEN TEA LEAF 0.5 mL/100 mL; CARBOMER 940 0.4 mL/100 mL; CETOSTEARYL ALCOHOL 1 mL/100 mL; CETEARYL GLUCOSIDE 1 mL/100 mL; CITRUS AURANTIUM FRUIT 0.5 mL/100 mL; GRAPEFRUIT 0.5 mL/100 mL; DIMETHYL SULFONE 3.5 mL/100 mL; ETHYLHEXYLGLYCERIN 0.3 mL/100 mL; GLYCERIN 3 mL/100 mL; ILEX PARAGUARIENSIS LEAF 0.5 mL/100 mL; PHENOXYETHANOL 0.7 mL/100 mL; ROSA CANINA FLOWER 0.5 mL/100 mL; .ALPHA.-TOCOPHEROL ACETATE, DL- 0.5 mL/100 mL; TROLAMINE 0.5 mL/100 mL; YUCCA SCHIDIGERA 0.5 mL/100 mL

Cryoderm Heat Warming Lotion

Directions

Adults and children 2 years and older:
Massage a small amount of lotion directly on the skin over the affected area. Repeat as necessary but do not apply more than 4 times daily.
Children under 2 years of age: Consult a Physician

Active Ingredient

Menthol USP 3.85%
Camphor USP 3.85%
Capsaicin USP 0.0355%

Inactive Ingredients

Aloe Vera, Arnica Extract, Boswellia Serrata Extract, Green Tea Extract, Carbomer, Cetearyl Alcohol, Cetearyl Glucoside, Orange Fruit Extract, Grapefruit Extract, Dimethyl Sulfone, Ethylhexylglycerin, Glycerin, Ilex Paraguariensis Leaf Extract, Phenoxyethanol, Purified Water, Rose Extract, Vitamin E, Triethanolamine, Yucca Extract

Other Information

Store in a cool dry place with lid or cap closed tightly.
Flammable: Keep away from excessive heat or open flame

Keep Out of Reach of Children

In case of accidental ingestion get medical help or contact a Poison Control Center immediately

Purpose

Pain Reliever

Uses

Temporary relieves minor aches and pains associated with

- sore muscles and joints
- arthritis
- backache
- muscle strains
- sprains
- bruises

Warnings

For external use only

When using this product:

Use only as directed. Do not bandage or use a heating pad or device. Avoid contact with eyes and mucous membranes. Do not apply to open wounds or damaged skin. Do not use with other ointment, creams, sprays or liniments. After applying wash hands thoroughly with cool water

Stop use and ask a doctor if:

Condition worsens or symptoms persist for more than 7 days or clear up and recur. Redness is present or irritatio develops

If pregnant or Breast Feeding:

Ask a health professional before use

this product contains Capsaicin

and may cause temporary burning, stinging, inflammation, redness or welts on the application site thatususally disappear in a few days. If you experience any of these symptoms discontinue use and contact your doctor immediately

PACKAGE LABEL

CryoDerm

HEAT

PAIN RELIEVING

WARM Therapy

Lotion

Fast, Deep Penetrating Pain Relief for:

Muscle Strains, Joint Pain, Backache, Arthritis, Sprained Ligaments & Bruises

Paraben Free / Propylene Glycol Free / Aspirin Free
NSAID Free / Silicone Dioxide Free / Gluten Free

Contains Essential Oils & Natural Extracts

MSM Arnica Boswellia Ilex

Active Ingredients:
Menthol . Camphor . Capsaicin

16 fl.oz. 449mL